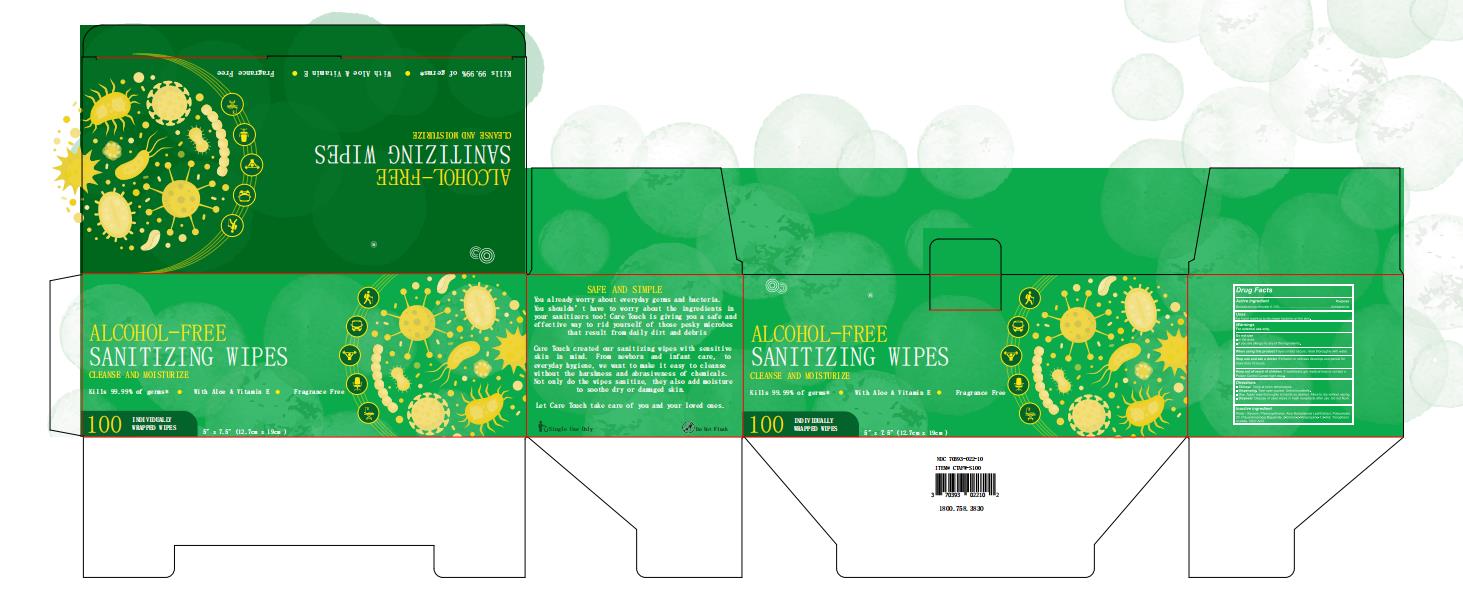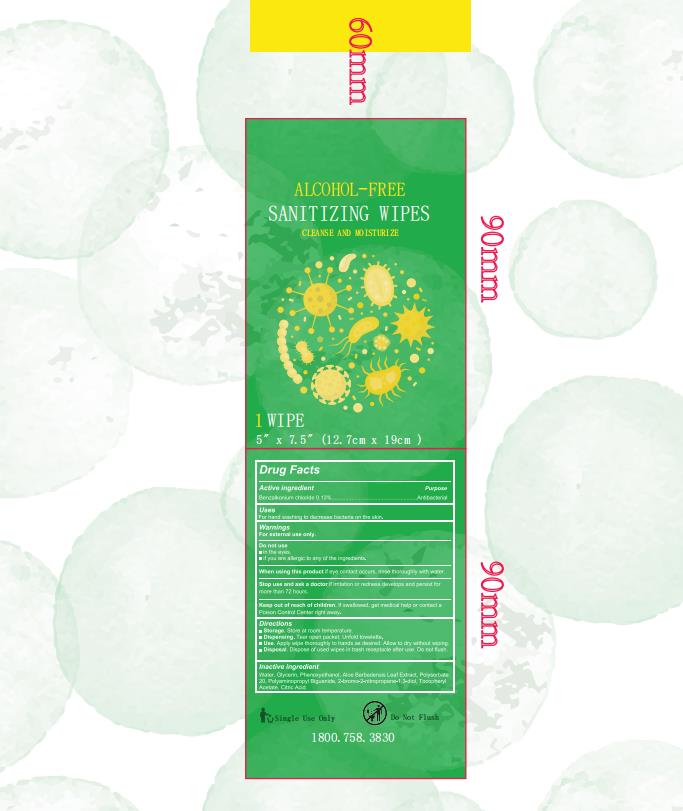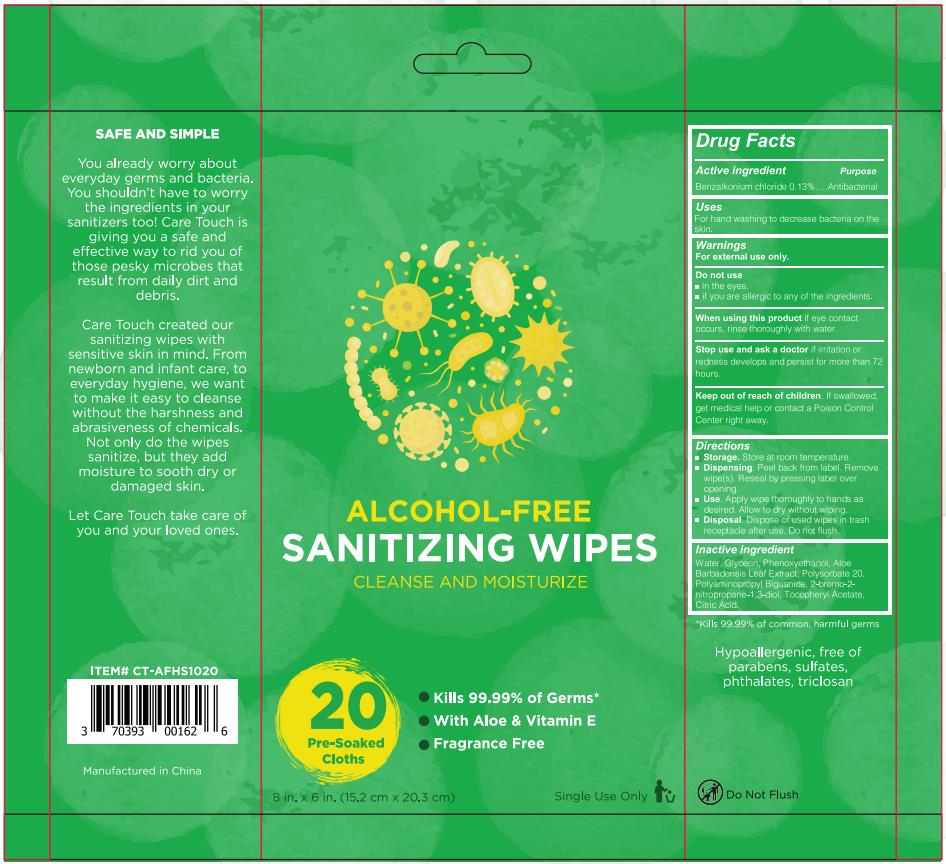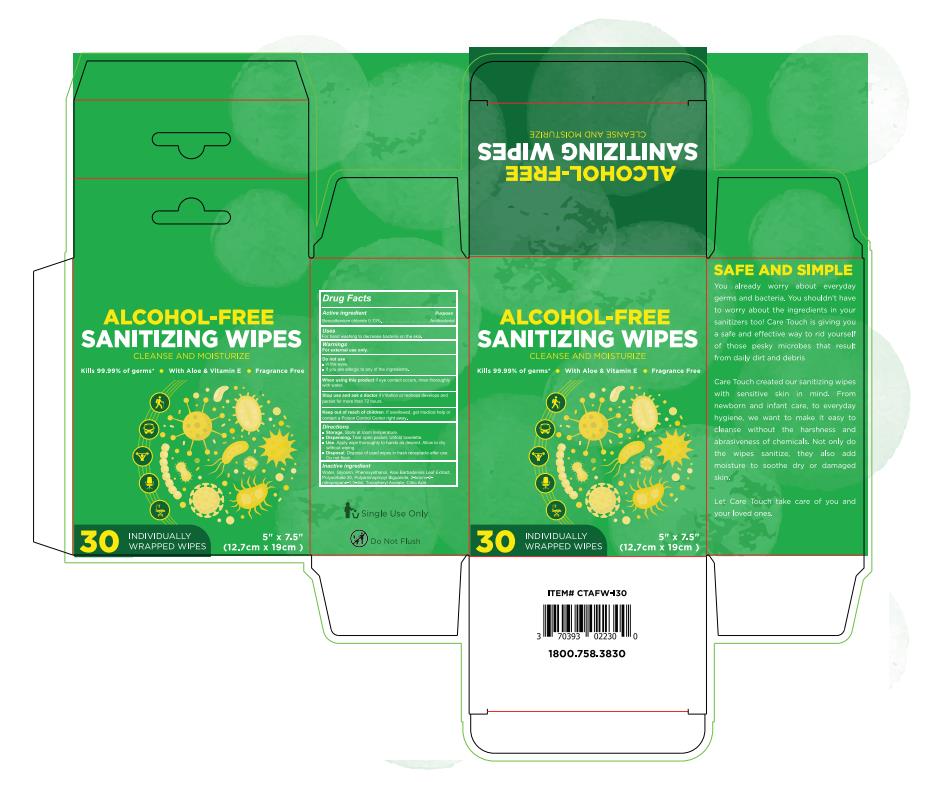 DRUG LABEL: Sanitizing Wipes
NDC: 78936-005 | Form: CLOTH
Manufacturer: Hangzhou Caring Cleaning Commodity Co.,Ltd
Category: otc | Type: HUMAN OTC DRUG LABEL
Date: 20200707

ACTIVE INGREDIENTS: BENZALKONIUM CHLORIDE 1.3 mg/100 mg
INACTIVE INGREDIENTS: CITRIC ACID ACETATE; POLYSORBATE 20; POLYAMINOPROPYL BIGUANIDE; ALOE VERA LEAF; ALPHA-TOCOPHEROL ACETATE; WATER; GLYCERIN; PHENOXYETHANOL; BRONOPOL

Sanitizing Wipes

Active Ingredient(s)

Benzalkonium Chloride 0.13% 1.3mg/mL.......Antibacterial

Purpose

Antiseptic

Use

For hand washing to decreases bacteria on skin.

Warnings

For external use only.

When using this product if eye contact occurs, rinse thoroughly with water.

Do not use

- in the eyes
- if you are allergic to any of the ingredient

Stop use and ask a doctor if irritation or redness develops and persist for more than 72 hours,

Keep out of reach of children. If swallowed, get medical help or contact a Poison Control Center right away.

Inactive ingredients

Water,Glycerin, Phenoxyethanol,Aloe Barbadensis Leaf Extract,Polysorbate 20, Polyaminopropyl Biguanide, 2-bromo-2-nitropropane-1,3-diol,Tocopheryl Acetate, Citric Acid.

Directions

- Storage.Store at room temperature.
- Dispensing.Tear open packet.Unfold towelette.
- Use.Apply wipe thoroughly to hands as desired.Allow to dry without wiping.
- Disposal.Dispose of used wipes in trash receptacle after use.Do not flush.

Package Label - Principal Display Panel

20 POUCH IN 1 BAG NDC: 78936-005-01

1 POUCH IN 1 PACKAGE/30 PACKAGES IN 1 BOX NDC: 78936-005-02

1 POUCH IN 1 PACKAGE/100 PACKAGES IN 1 BOX NDC: 78936-005-03